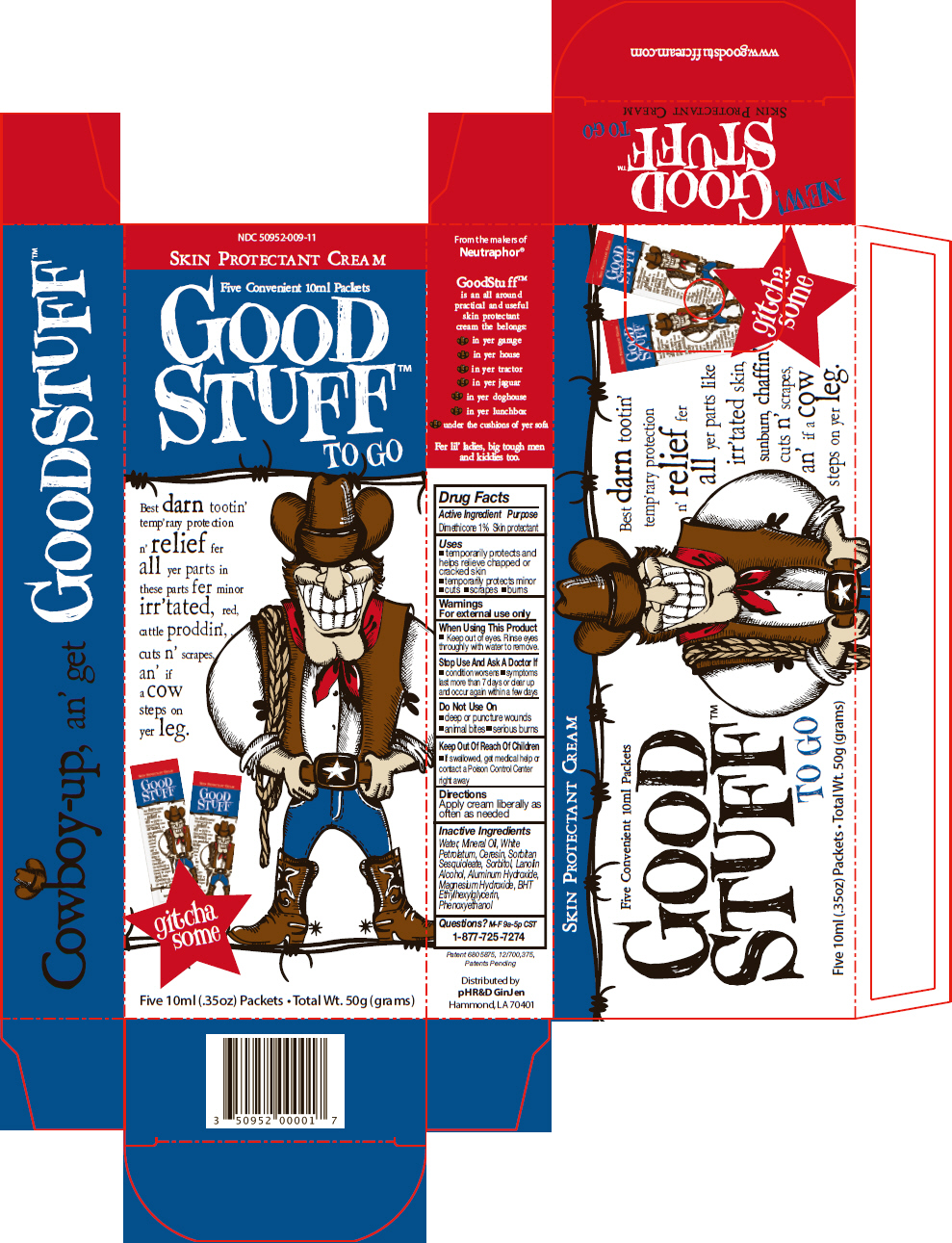 DRUG LABEL: GoodStuff 
NDC: 50952-009 | Form: CREAM
Manufacturer: pH R&D LLC
Category: otc | Type: HUMAN OTC DRUG LABEL
Date: 20130703

ACTIVE INGREDIENTS: Dimethicone 10 mg/1 g
INACTIVE INGREDIENTS: Water; Mineral Oil; Petrolatum; Ceresin; Sorbitan Sesquioleate; Sorbitol; Lanolin Alcohols; Aluminum Hydroxide; Magnesium Hydroxide; Butylated Hydroxytoluene; Ethylhexylglycerin; Phenoxyethanol

GoodStuff™
Skin Protectant Cream

Drug Facts

Active Ingredient

Dimethicone 1%

Purpose

Skin protectant

Uses

- temporarily protects and helps relieve chapped or cracked skin
- temporarily protects minor
  - cuts
  - scrapes
  - burns

Warnings

For external use only

When Using This Product

- Keep out of eyes. Rinse eyes throughly with water to remove.

Stop Use And Ask A Doctor If

- condition worsens
- symptoms last more than 7 days or clear up and occur again within a few days

Do Not Use On

- deep or puncture wounds
- animal bites
- serious burns

Keep Out Of Reach Of Children

- If swallowed, get medical help or contact a Poison Control Center right away

Directions

Apply cream liberally as often as needed

Inactive Ingredients

Water, Mineral Oil, White Petrolatum, Ceresin, Sorbitan Sesquioleate, Sorbitol, Lanolin Alcohol, Aluminum Hydroxide, Magnesium Hydroxide, BHT Ethylhexylglycerin, Phenoxyethanol

Questions?

M-F 9a-5p CST
1-877-725-7274

Distributed by
pH R&D GinJen
Hammond, LA 70401

PRINCIPAL DISPLAY PANEL - 5 Packet Carton

NDC 50952-009-11

SKIN PROTECTANT CREAM

Five Convenient 10ml Packets

GOOD
STUFF™
TO GO

Best darn tootin'
temp'rary protection
n' relief fer
all yer parts in
these parts fer minor
irr'tated, red,
cattle proddin', ,
cuts n' scrapes,
an' if
a cow
steps on
yer leg.

gitcha
some

Five 10ml (.35oz) Packets • Total Wt. 50g (grams)